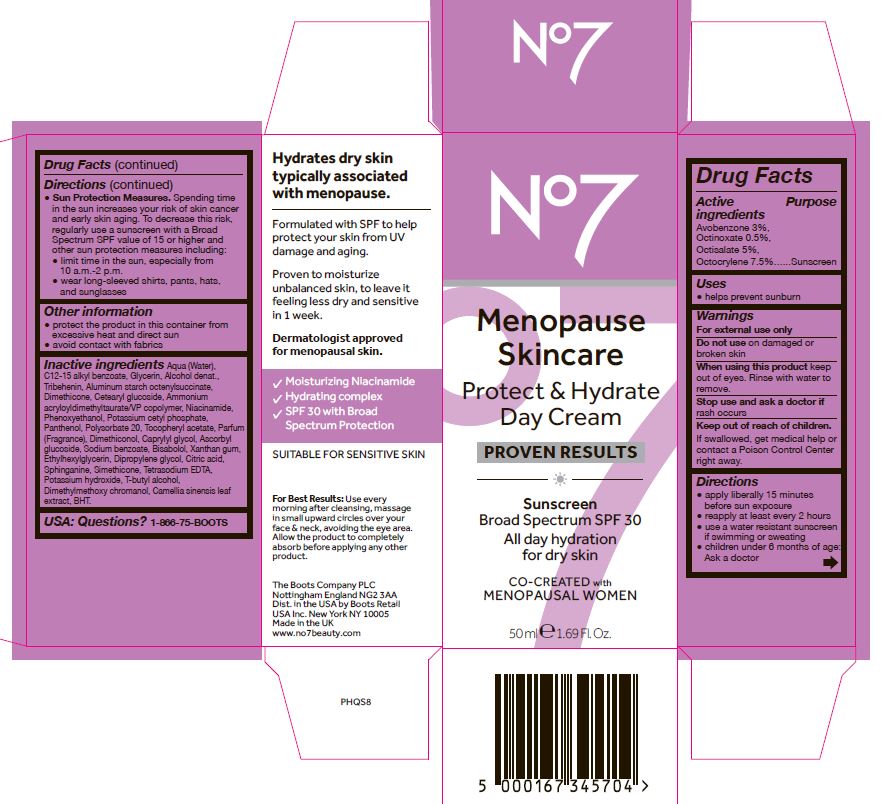 DRUG LABEL: No7 Menopause Skincare Protect and Hydrate Day Cream Sunscreen Broad Spectrum SPF 30
NDC: 11489-188 | Form: CREAM
Manufacturer: BCM Ltd
Category: otc | Type: HUMAN OTC DRUG LABEL
Date: 20220301

ACTIVE INGREDIENTS: AVOBENZONE 1.5 g/1 g; OCTOCRYLENE 3.75 g/1 g; OCTISALATE 2.5 g/1 g; OCTINOXATE 0.25 g/1 g
INACTIVE INGREDIENTS: WATER; GLYCERIN; ALUMINUM STARCH OCTENYLSUCCINATE; CETEARYL GLUCOSIDE; TRIBEHENIN; DIMETHICONE; AMMONIUM ACRYLOYLDIMETHYLTAURATE/VP COPOLYMER; PHENOXYETHANOL; POTASSIUM CETYL PHOSPHATE; DIMETHICONOL (100000 CST); DIPROPYLENE GLYCOL; XANTHAN GUM; ASCORBYL GLUCOSIDE; EDETATE SODIUM; TERT-BUTYL ALCOHOL; DIMETHYLMETHOXY CHROMANOL; POLYSORBATE 20; POTASSIUM HYDROXIDE; SODIUM BENZOATE; SPHINGANINE; ETHYLHEXYLGLYCERIN; BENZOIC ACID; ALCOHOL; NIACINAMIDE; PANTHENOL; ALPHA-TOCOPHEROL ACETATE; CAPRYLYL GLYCOL; .ALPHA.-BISABOLOL, (+)-; CITRIC ACID MONOHYDRATE; CAMELLIA SINENSIS WHOLE; BUTYLATED HYDROXYTOLUENE; BENZYL ALCOHOL

No7 Menopause Skincare Protect and Hydrate Day Cream Sunscreen Broad Spectrum SPF 30

Active Ingredients

Avobenzone 3%

Octinoxate 0.5%

Octisalate 5%

Octocrylene 7.5%

Purpose

Sunscreen

Uses

helps prevent sunburn

Warnings

For external use only

Do not use on damaged or broken skin

When using this product keep out of eyes. Rinse with water to remove.

Ask a doctor

Stop use and ask a doctor if rash occurs

Keep out of reach of children. If swallowed, get medical help or contact a Poison Control Center right away.

Directions

apply liberally 15 minutes before sun exposure

reapply at least every 2 hours

use a water resistant sunscreen if swimming or sweating

children under 6 months of age: Ask a doctor

Sun Protection Measures. Spending time in the sun increases your risk of skin cancer and early skin aging. To decrease this risk, regularly use a sunscreen with a Broad Spectrum SPF value of 15 or higher and other sun protection measures including:

limit time in the sun, especially from 10 a.m - 2 p.m.

wear long-sleeved shirts, pants, hats and sunglasses

Storage

Other information

protect the product in this container from excessive heat and direct sun

avoid contact with fabrics

Inactive ingredients

Aqua (Water), C12-15 alkyl benzoate, Glycerin, Alcohol denat., Tribehenin, Aluminum starch octenylsuccinate, Dimethicone, Cetearyl glucoside, Ammonium acryloyldimethyltaurate/VP copolymer, Niacinamide, Phenoxyethanol, Potassium cetyl phosphate, Panthenol, Polysorbate 20, Tocopheryl acetate, Parfum (Fragrance), Dimethiconol, Caprylyl glycol, Ascorbyl glucoside, Sodium benzoate, Bisabolol, Xanthan gum, Ethylhexylglycerin, Dipropylene glycol, Citric acid, Sphinganine, Simethicone, Tetrasodium EDTA, Potassium hydroxide, T-butyl alcohol, Dimethylmethoxy chromanol, Camellia sinensis leaf extract, BHT.

Description

All day hydration for dry skin

CO-CREATED with MENOPAUSAL WOMEN

Hydrates skin sypically associated with menopause.

Formulated with SPF to help protect your skin from UV damage and aging.

Proven to moisturize unbalanced skin, to leave it feeling less dry and sensitive in 1 week.

Dermatologist approved for menopausal skin.

Moisturizing Niacinamide

Hydrating complex

SPF 30 with Broad Spectrum Protection

SUITABLE FOR SENSITIVE SKIN

PATIENT COUNSELING INFORMATION

The Boots Company PLC

Nottingham England NG2 3AA

Dist. in the USA by Boots Retail USA Inc. New York NY 10005

Made in the UK

www.No7beauty.com

Carton